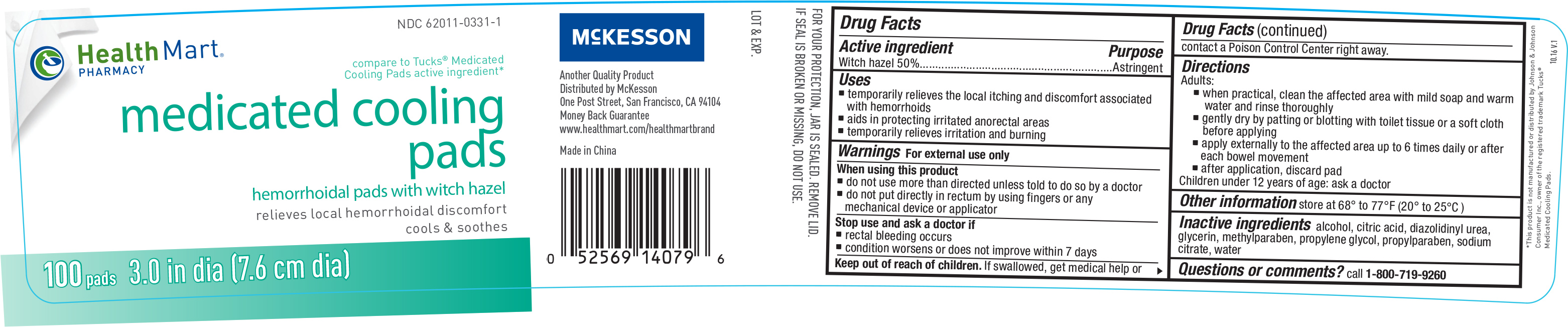 DRUG LABEL: Health Mart Medicated Cooling
NDC: 62011-0331 | Form: CLOTH
Manufacturer: Mckesson (Health Mart)
Category: otc | Type: HUMAN OTC DRUG LABEL
Date: 20170329

ACTIVE INGREDIENTS: WITCH HAZEL 500 mg/1 1
INACTIVE INGREDIENTS: ALCOHOL; CITRIC ACID MONOHYDRATE; DIAZOLIDINYL UREA; GLYCERIN; METHYLPARABEN; PROPYLENE GLYCOL; PROPYLPARABEN; SODIUM CITRATE; WATER

Active ingredient Purpose

Witch hazel 50%..........................................Astringent

Uses

- temporarily relieves the local itching and discomfort associated with hemorrhoids
- aids in protecting irritated anorectal areas
- temporarily relieves irritation and burning

Warnings

For external use only

When using this product

- do not use more than directed unless told to do so by a doctor
- do not put directly in rectum by using fingers or any mechanical deviec or applicator

Stop use and ask a doctor if

- rectal bleeding occurs
- condition worsens or does not improve within 7 days

Keep out of reach of children. If swallowed, get medical help or contact a Poison Control Center right away.

Directions

Adults:

- when practical, clean the affected area with mild soap and warm water and rinse thoroughly
- gently dry by patting or blotting with toilet tissue or a soft cloth before applying
- apply externally to the affected area up to 6 times daily or after each bowl movement
- after application, discard pad

Children under 12 years of age: ask a doctor

Other information store at 68° to 77°F (20° to 25°C)

Inactive ingredients

alcohol, citric acid, diazolidinyl urea, glycerin, methylparaben, propylene glycol, propylparaben, sodium citrate, water

DOSAGE AND ADMINISTRATION

Distributed by:

Mckesson

One Post Street

San Francisco, CA 94104

www.healthmart.com/healthmartbrand

Made in China